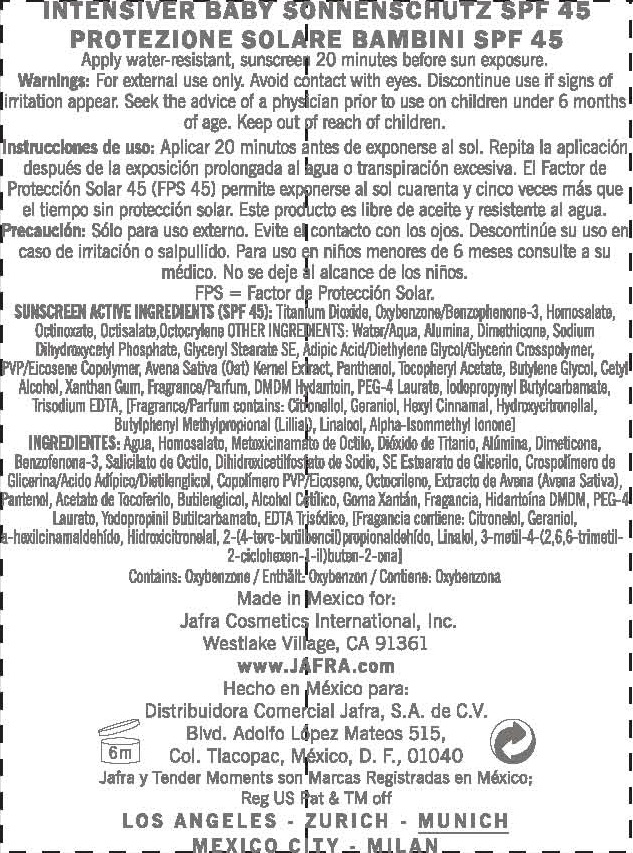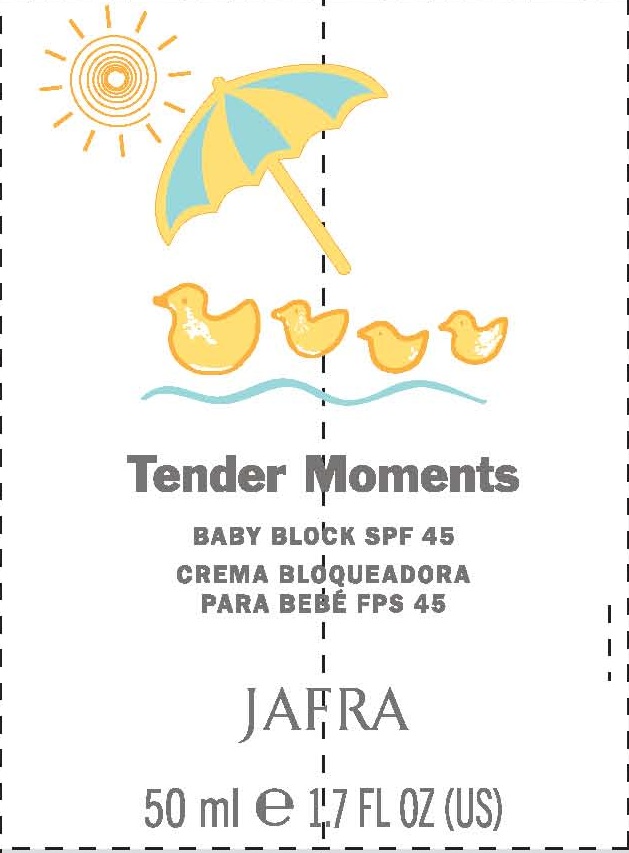 DRUG LABEL: TENDER MOMENTS
NDC: 68828-060 | Form: LOTION
Manufacturer: JAFRA COSMETICS INTERNATIONAL
Category: otc | Type: HUMAN OTC DRUG LABEL
Date: 20120516

ACTIVE INGREDIENTS: HOMOSALATE 10 g/100 mL; OCTINOXATE 7.7 g/100 mL; OCTISALATE 5 g/100 mL; OCTOCRYLENE 1.5 g/100 mL; TITANIUM DIOXIDE 5.5 g/100 mL; OXYBENZONE 5 g/100 mL
INACTIVE INGREDIENTS: WATER; ALUMINUM OXIDE; DIMETHICONE; GLYCERYL STEARATE SE; SODIUM PHOSPHATE, MONOBASIC; BUTYLENE GLYCOL; DIETHYLENE GLYCOL ADIPATE; OAT; POVIDONE K30; CETYL ALCOHOL; PEG-4 LAURATE; DMDM HYDANTOIN; IODOPROPYNYL BUTYLCARBAMATE; PANTHENOL; .ALPHA.-TOCOPHEROL ACETATE; XANTHAN GUM; EDETATE TRISODIUM

TENDER MOMENTS SPF 45

ACTIVE INGREDIENT

SUNSCREEN ACTIVE INGREDIENT (SPF 45): TITANIUM DIOXIDE, OXYBENZONE/BENZOPHENONE-3, HOMOSALATE, OCTINOXATE, OCTISALATE, OCTOCRYLENE

PURPOSE: SUNSCREEN

INACTIVE INGREDIENT

OTHER INGREDIENTS: WATER/AQUA, ALUMINA, DIMETHICONE, SODIUM DIHYDROXYCETYL PHOSPHATE, GLYCERYL STEARATE SE, ADIPIC ACID/DIETHYLENE GLYCOL/GLYCERIN CROSSPOLYMER, PVP/EICOSENE COPOLYMER, AVENA SATIVA (OAT) KERNEL EXTRACT, PANTHENOL, TOCOPHERYL ACETATE, BUTYLENE GLYCOL, CETYL ALCOHOL, XANTHAN GUM, FRAGRANCE/PARFUM, DMDM HYDANTOIN, PEG-4 LAURATE, IODOPROPYNYL BUTYLCARBAMATE, TRISODIUM EDTA, [FRAGRANCE/PARFUM CONTAINS: CITRONELLOL, GERANIOL, HEXYL CINNAMAL, HYDROXYCITRONELLOL, BUTYLPHENYL METHYLPROPIONAL (LILLIAL), LINALOL, ALPHA-ISOMMETHYL IONONE]

INDICATIONS AND USAGE

BABY BLOCK SPF 45

DOSAGE AND ADMINISTRATION

APPLY WATER-RESISTANT SUNSCREEN 20 MINUTES BEFORE SUN EXPOSURE.

DISCONTINUE USE IF SIGNS OF IRRITATION APPEAR.

KEEP OUT OF REACH OF CHILDREN.

PACKAGE LABEL

TENDER MOMENTS
BABY BLOCK SPF 45
JAFRA

WARNINGS

WARNINGS: FOR EXTERNAL USE ONLY. AVOID CONTACT WITH EYES.

PEDIATRIC USE

SEEK THE ADVICE OF A PHYSICIAN PRIOR TO USE ON CHILDREN UNDER 6 MONTHS OF AGE.